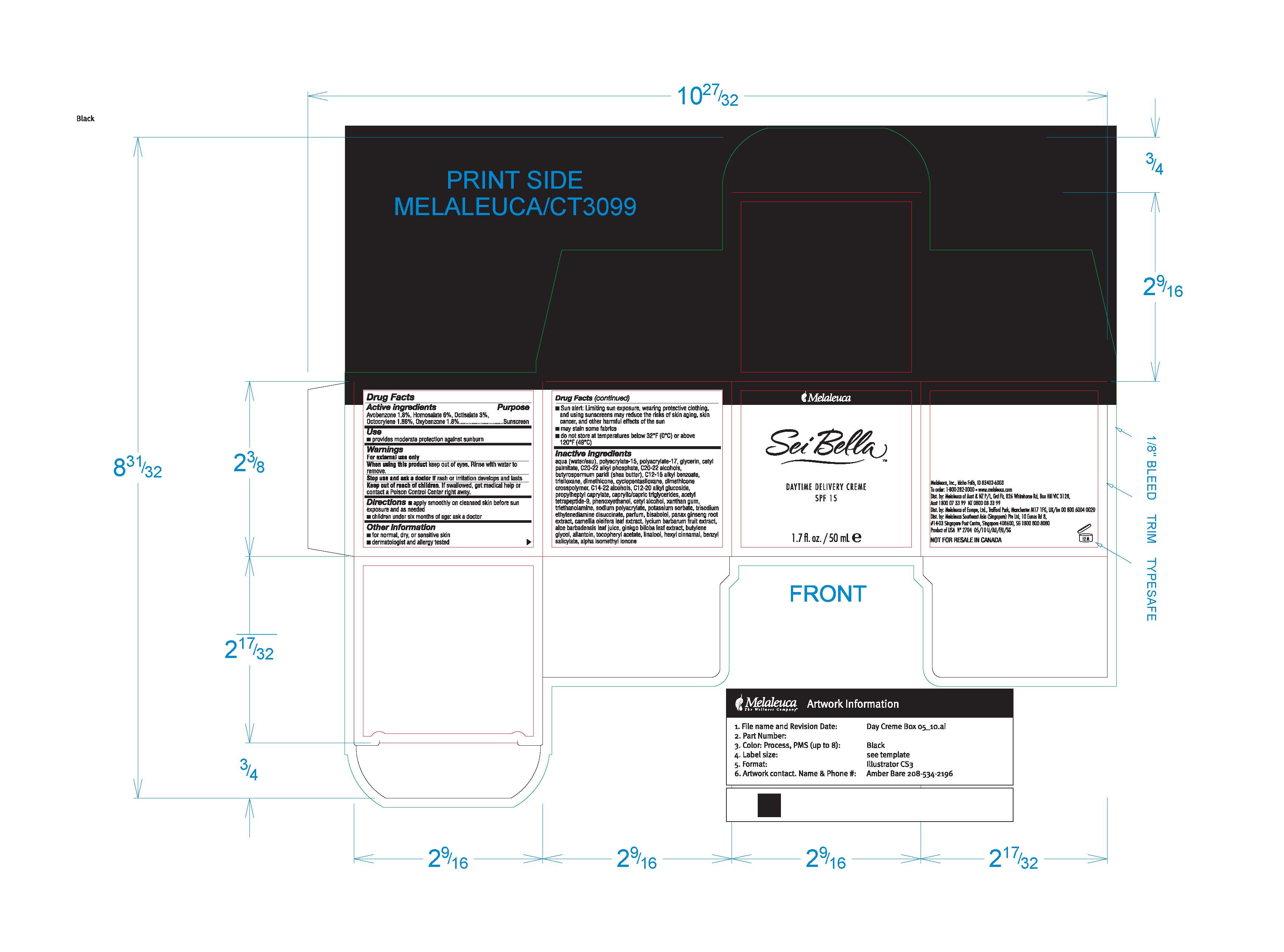 DRUG LABEL: Sei Bella
NDC: 54473-186 | Form: CREAM
Manufacturer: Melaleuca, Inc.
Category: otc | Type: HUMAN OTC DRUG LABEL
Date: 20110126

ACTIVE INGREDIENTS: AVOBENZONE 0.9 g/50 mL; HOMOSALATE 3 g/50 mL; OCTISALATE 1.5 g/50 mL; OCTOCRYLENE 0.93 g/50 mL; Oxybenzone 0.9 g/50 mL
INACTIVE INGREDIENTS: Water; Glycerin; CETYL PALMITATE; SHEA BUTTER; C12-15 ALKYL BENZOATE; TRISILOXANE; DIMETHICONE; Cyclomethicone 5; C14-22 ALCOHOLS; MEDIUM-CHAIN TRIGLYCERIDES; PHENOXYETHANOL; Cetyl Alcohol; XANTHAN GUM; Trolamine; POTASSIUM SORBATE; LEVOMENOL; CAMELLIA OLEIFERA LEAF; ALOE VERA LEAF; GINKGO; BUTYLENE GLYCOL; ALLANTOIN; ALPHA-TOCOPHEROL ACETATE; ASIAN GINSENG

Sei Bella Daytime Delivery Creme Content of Label

Active ingredients
Avobenzone 1.8%, Homosalate 6%, Octisalate, 3%, Octocrylene 1.86%, Oxybenzone 1.8%

Purpose
Sunscreen

Use

- provides moderate protection against sunburn

Warnings
For external use only

When using this product keep out of eyes. Rinse with water to remove.

Stop use and ask a doctor if rash or irritation develops and lasts

Keep out of reach of children. If swallowed, get medical help or contact a Poison Control Center right away.

Directions

- apply smoothly on cleansed skin before sun exposure and as needed
- children under six months of age: ask a doctor

Other information

- dermatologist and allergy tested

Other information

- Sun alert: Limiting sun exposure, wearing protective clothing, and using sunscreens may reduce the risks of skin aging, skin cancer, and other harmful effects of the sun
- may stain some fabrics

Other information

- do not store at temperatures below 32°F (0°C) or above 120°F (49°C)

Inactive ingredients
aqua (water/eau), polyacrylate-15, polyacrylate-17, glycerin, cetyl palmitate, C20-22 alkyl phosphate, C20-22 alcohols, butyrospermum parkii (shea butter), C12-15 alkyl benzoate, trisiloxane, dimethicone, cyclopentasiloxane, dimethicone crosspolymer, C14-22 alcohols, C12-20 alkyl glucoside, propylheptyl caprylate, caprylic/capric triglycerides, acetyl tetrapeptide-9, phenoxyethanol, cetyl alcohol, xanthan gum, triethanolamine, sodium polyacrylate, potassium sorbate, trisodium ethylenediamine disuccinate, parfum, bisabolol, panax ginseng root extract, camellia oleifera leaf extract, lycium barbarum fruit extract, aloe barbadensis leaf juice, ginkgo biloba leaf extract, butylene glycol, allantoin, tocopheryl acetate, linalool, hexyl cinnamal, benzyl salicylate, alpha isomethyl ionone